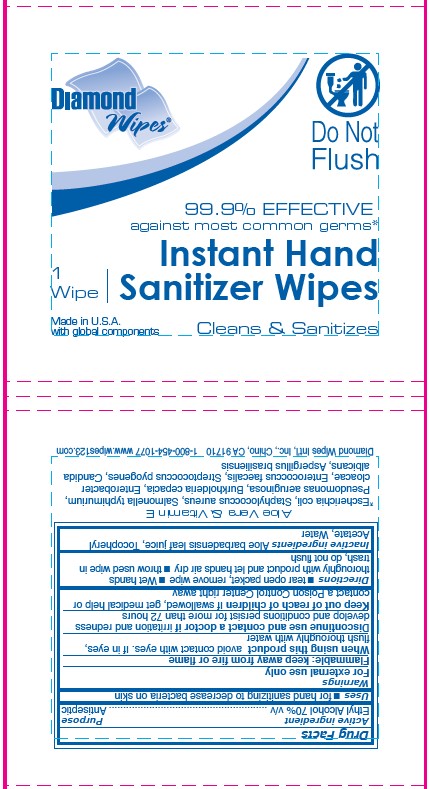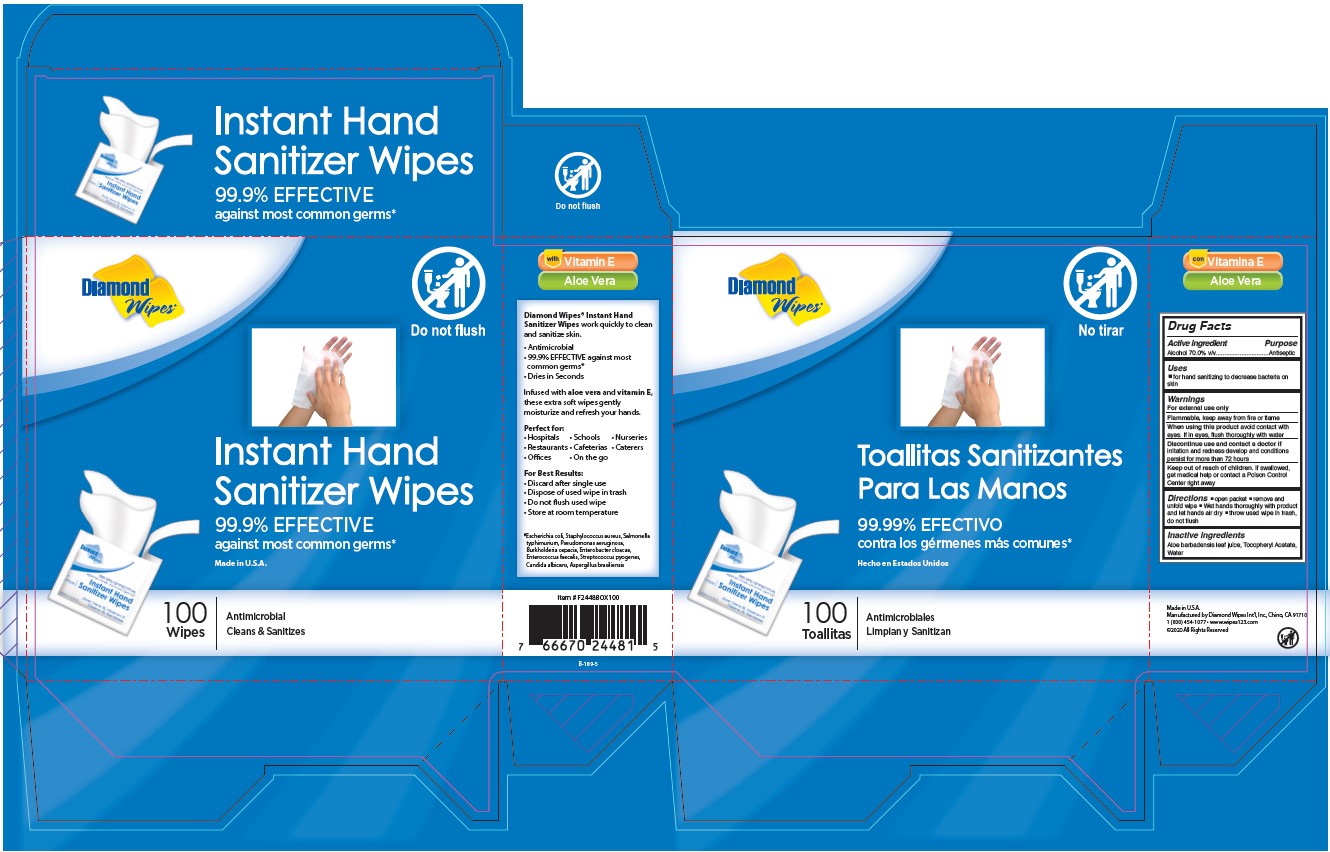 DRUG LABEL: INSTANT HAND SANITIZER WIPES
NDC: 64709-185 | Form: CLOTH
Manufacturer: Diamond Wipes International, Inc.
Category: otc | Type: HUMAN OTC DRUG LABEL
Date: 20250819

ACTIVE INGREDIENTS: ALCOHOL 70 mL/100 mL
INACTIVE INGREDIENTS: WATER; ALOE VERA LEAF; .ALPHA.-TOCOPHEROL ACETATE

INSTANT HAND SANITIZWER WIPES

Active Ingredient

Ethyl Alcohol 70% v/v

Purpose

Antiseptic

Uses

■ for hand sanitizing to decrease bacteria on skin

Warnings

For external use only

Flammable, keep away from fire or flame

When using this product avoid contact with eyes. If in eyes, flush thoroughly with water

Discontinue use and contact a doctor if irritation and redness develop and conditions persist for more than 72 hours

Keep out of reach of children

If swallowed, get medical help or contact a Poison Control Center right away

Directions

■ tear open packet, remove wipe ■ Wet hands thoroughly with product and let hands air dry ■ throw used wipe in trash, do not flush

Inactive ingredients

Aloe Barbadensis Leaf Juice, Tocopheryl Acetate, Water

Label

Diamond Wipes®

Do Not Flush

99.9% EFFECTIVE against most common germs*

1 Wipe| Instant Hand Sanitizer Wipes

Made in U.S.A. with global components Cleans & Sanitizes

Drug Facts
Active ingredient Purpose
Ethyl Alcohol 70% v/v.................Antiseptic

Uses ■for hand sanitizing to decrease bacteria on skin
Warnings
For external use only
Flammable: keep away from fire or flame
When using this product avoid contact with eyes. If in eyes, flush thoroughly with water
Discontinue use and contact a doctor if irritation and redness develop and conditions persist for more than 72 hours
Keep out of reach of children If swallowed, get medical help or contact a Poison Control Center right away

Directions ■tear open packet, remove wipe ■Wet hands thoroughly with product and let hands air dry ■throw used wipe in

trash, do not flush
Inactive ingredients Aloe barbadensis leaf juice, Tocopheryl Acetate, Water
Aloe Vera & Vitamin E

*Escherichia coli, Staphylococcus aureus, Salmonella typhimurium, Pseudomonas aeruginosa, Burkholderia cepacia, Enterobacter cloacae, Enterococcus faecalis, Streptococcus pyogenes, Candida albicans, Aspergillus brasiliensis

Diamond Wipes Int’l, Inc., Chino, CA 91710 1-800-454-1077 www.wipes123.com

Instant Hand Sanitizer Wipes

99.9% EFFECTIVE against most common germs*

Diamond Wipes®

Do not flush

Instant Hand Sanitizer Wipes

Kills 99.99% Germs

Made In U.S.A.

100 Wipes Antimicrobial Cleans & Sanitizes

with Vitamin E

Aloe Vera

Diamond Wipes® Instant Hand
Sanitizer Wipes work quickly to clean
and sanitize skin.
• Antimicrobial
• 99.9% EFFECTIVE against most
common germs*
• Dries in Seconds
Infused with aloe vera and vitamin E,
these extra soft wipes gently
moisturize and refresh your hands.
Perfect for:
• Hospitals • Schools • Nurseries
• Restaurants • Cafeterias • Caterers
• Offices • On the go
For Best Results:
• Discard after single use
• Dispose of used wipe in trash
• Do not fush used wipe
• Store at room temperature
*Escherichia coli, Staphylococcus aureus, Salmonella typhimurium, Pseudomonas aeruginosa, Burkholderia cepacia, Enterobacter cloacae, Enterococcus faecalis, Streptococcus pyogenes, Candida albicans, Aspergillus brasiliensis

Item # F2448BOX100

7 66670 24481 5

B-189-5

Diamond Wipes®

No tirar

Toallitas Sanitizantes Para Las Manos

99.99% EFECTIVO
contra los gérmenes más comunes*
Hecho en Estados Unidos

100 Toallitas Antimicrobiales Limpian y Sanitizan

con Vitamina E
Aloe Vera

Drug Facts
Active ingredient Purpose
Alcohol 70.0% v/v...............................Antiseptic
Uses
■ for hand sanitizing to decrease bacteria on skin
Warnings
For external use only
Flammable, keep away from fire or flame
When using this product avoid contact with eyes. If in eyes, flush thoroughly with water
Discontinue use and contact a doctor if irritation and redness develop and conditions persist for more than 72 hours
Keep out of reach of children. If swallowed, get medical help or contact a Poison Control Center right away
Directions ■ open packet ■ remove and unfold wipe ■ Wet hands thoroughly with product and let hands air dry ■ throw used wipe in trash, do not flush
Inactive ingredients
Aloe barbadensis leaf juice, Tocopheryl Acetate, Water

Made in U.S.A.
Manufactured by Diamond Wipes Int’l, Inc., Chino, CA 91710
1 (800) 454-1077 • www.wipes123.com
©2020 All Rights Reserved